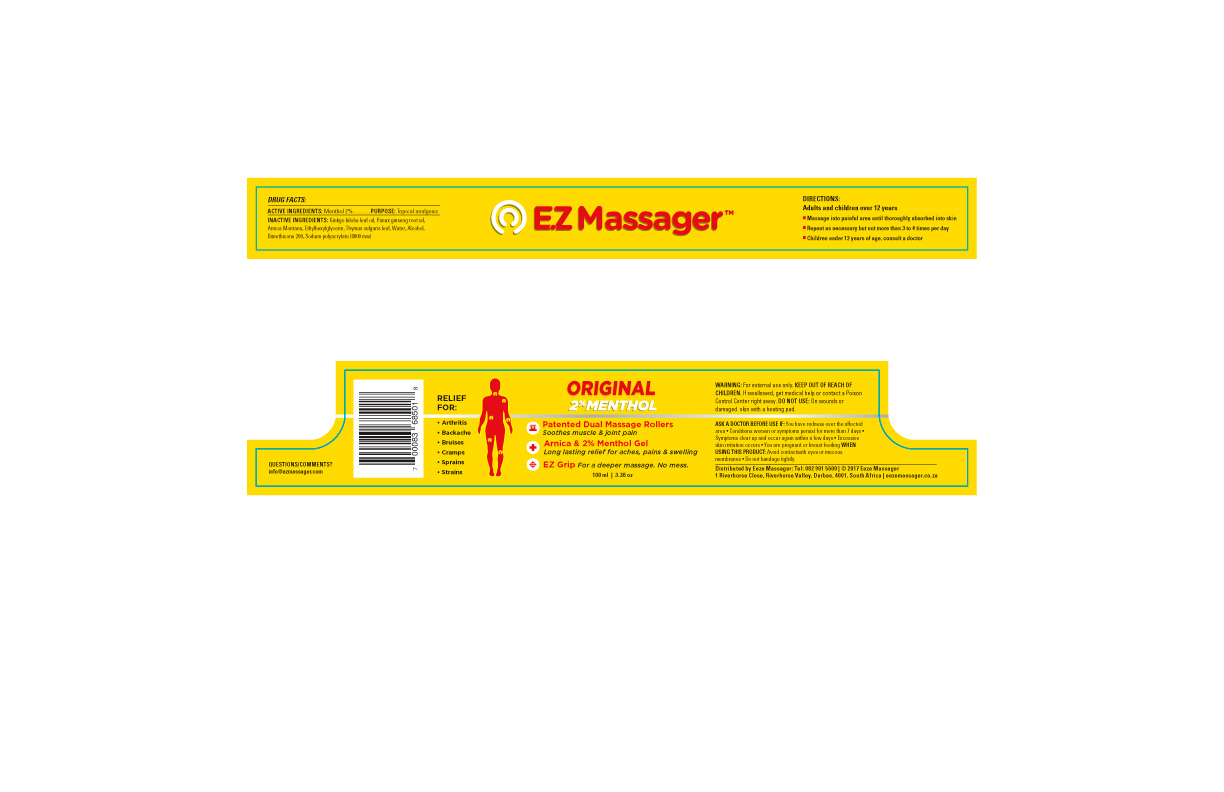 DRUG LABEL: Ez Massager 2
NDC: 71555-002 | Form: GEL
Manufacturer: BlackPort Distribution
Category: otc | Type: HUMAN OTC DRUG LABEL
Date: 20181009

ACTIVE INGREDIENTS: MENTHOL 2 g/100 mL
INACTIVE INGREDIENTS: ARNICA MONTANA; GINKGO BILOBA LEAF OIL; ETHYLHEXYLGLYCERIN; WATER; ALCOHOL; DIMETHICONE 200; SODIUM POLYACRYLATE (8000 MW); PANAX GINSENG ROOT OIL; THYMUS VULGARIS LEAF

DOSAGE AND ADMINISTRATION

- Massage into painful area until thoroughly absorbed into skin
- Repeat as necessary but not more than 3 to 4 times per day

WARNINGS

WARNING: For external use only

DO NOT USE: On wounds or damaged skin with a heating pad

ASK A DOCTOR BEFORE USE IF:

- You have redness over the affected area
- Conditions worsen or sypmtoms persist for more than 7 days
- Symptons clear up and occur again within a few days
- Excessive skin irritation occurs
- You are pregnant or breast feeding

INACTIVE INGREDIENT

Aqua/distilled/deionized

Rectified Alcohol

Arnica water-soluble

Beneficial Herbal Extract

Perservative 9010

INDICATIONS AND USAGE

Instant relief for:

Arthritis

Backache

Bruises

Cramps

Sprains

Strains

WHEN USING THIS PRODUCT:

- Avoid contact with eyes or mucous membranes
- Do not bandage tightly

PURPOSE

Topical Analgesic

KEEP OUT OF REACH OF CHILDREN: If swallowed, get medical help or contact a Poison Control Center right away.

ACTIVE INGREDIENT

Menthol, 2%

PACKAGE LABEL

Ez Massager 2